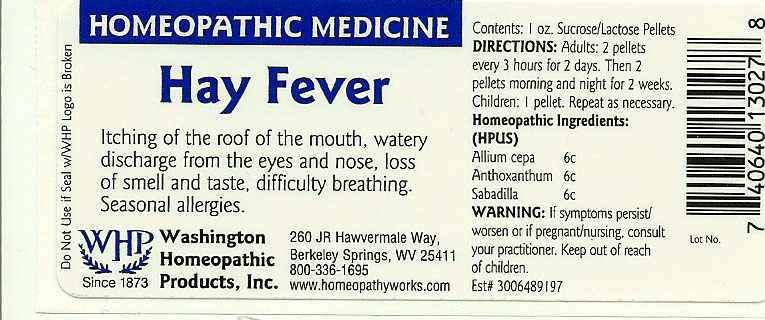 DRUG LABEL: Hay Fever
NDC: 68428-011 | Form: PELLET
Manufacturer: Washington Homeopathic Products
Category: homeopathic | Type: HUMAN OTC DRUG LABEL
Date: 20191223

ACTIVE INGREDIENTS: ONION 6 [hp_C]/28 g; ANTHOXANTHUM ODORATUM 6 [hp_C]/28 g; SCHOENOCAULON OFFICINALE SEED 6 [hp_C]/28 g
INACTIVE INGREDIENTS: SUCROSE; LACTOSE

DRUG FACTS

ACTIVE INGREDIENTS

ALLIUM CEPA 6C

ANTHOXANTHUM 6C

SABADILLA 6C

USES

To relieve the symptoms of itching of the roof of the mouth, watery discharge from the eyes and nose, loss of smell and taste, difficulty breathing. Seasonal Allergies.

KEEP OUT OF REACH OF CHILDREN

Keep this and all medicines out of reach of children.

INDICATIONS

ALLIUM CEPA Head cold

ANTHOXANTHUM Hay fever

SABADILLA Hay fever

STOP USE AND ASK DOCTOR

If symptoms persist/worsen or if pregnant/nursing, stop use and consult your practitioner.

DIRECTIONS

Adults 2 pellets every 3 hours for 2 days. Then 2 pellets morning and night for 2 weeks.

Children: 1 pellet. Repeat as necessary.

INACTIVE INGREDIENTS

Sucrose/Lactose

PRINCIPAL DISPLAY PANEL

Enter section text here